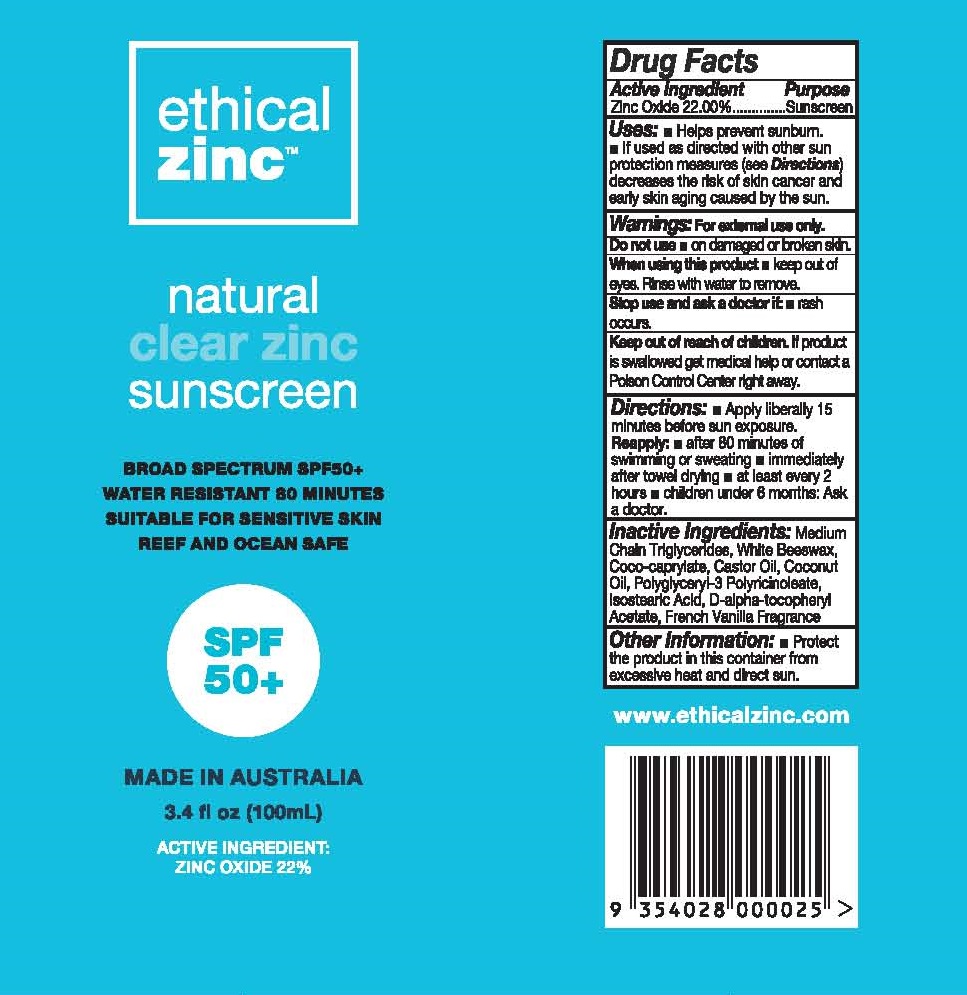 DRUG LABEL: ETHICAL ZINC NATURAL CLEAR ZINC SUNSCREEN


NDC: 72962-101 | Form: LOTION
Manufacturer: ETHICAL ZINC PTY LTD
Category: otc | Type: HUMAN OTC DRUG LABEL
Date: 20230925

ACTIVE INGREDIENTS: ZINC OXIDE 22 g/100 mL
INACTIVE INGREDIENTS: MEDIUM-CHAIN TRIGLYCERIDES; WHITE WAX; COCO-CAPRYLATE; CASTOR OIL; COCONUT OIL; POLYGLYCERYL-3 RICINOLEATE; ISOSTEARIC ACID; .ALPHA.-TOCOPHEROL ACETATE

ETHICAL ZINC - NATURAL CLEAR ZINC SUNSCREEN SPF-50 (72962-101)

ACTIVE INGREDIENTS

ZINC OXIDE 22.00%

PURPOSE

SUNSCREEN

USE

- HELPS PREVENT SUNBURN.
- IF USED AS DIRECTED WITH OTHER SUN PROTECTION MEASURES (SEE DIRECTIONS) DECREASES THE RISK OF CANCER AND EARLY SKIN AGING CAUSED BY THE SUN.

WARNINGS

FOR EXTERNAL USE ONLY.

DO NOT USE : ON DAMAGED OR BROKEN SKIN.

WHEN USING THIS PRODUCT: KEEP OUT OF EYES. RINSE WITH WATER TO REMOVE.

STOP USE AND ASK A DOCTOR IF : RASH OCCURS.

KEEP OUT OF REACH OF CHILDREN. IF PRODUCT IS SWALLOWED, GET MEDICAL HELP OR CONTACT A POISON CONTROL CENTER RIGHT AWAY.

DIRECTIONS

- APPLY LIBERALLY 15 MINUTES BEFORE SUN EXPOSURE.

REAPPLY:

- AFTER 80 MINUTES OF SWIMMING OR SWEATING
- IMMEDIATELY AFTER TOWEL DRYING
- AT LEAST EVERY 2 HOURS
- CHILDREN UNDER 6 MONTHS: ASK A DOCTOR.

INACTIVE INGREDIENTS

MEDIUM CHAIN TRIGLYCERIDES, WHITE BEESWAX, COCO-CAPRYLATE, CASTOR OIL, COCONUT OIL, POLYGLYCERYL-3 POLYRICINOLEATE, ISOSTEARIC ACID, D-ALPHA-TOCOPHERYL ACETATE, FRENCH VANILLA FRAGRANCE

OTHER INFORMATION

- PROTECT THE PRODUCT IN THIS CONTAINER FROM EXCESSIVE HEAT AND DIRECT SUN.